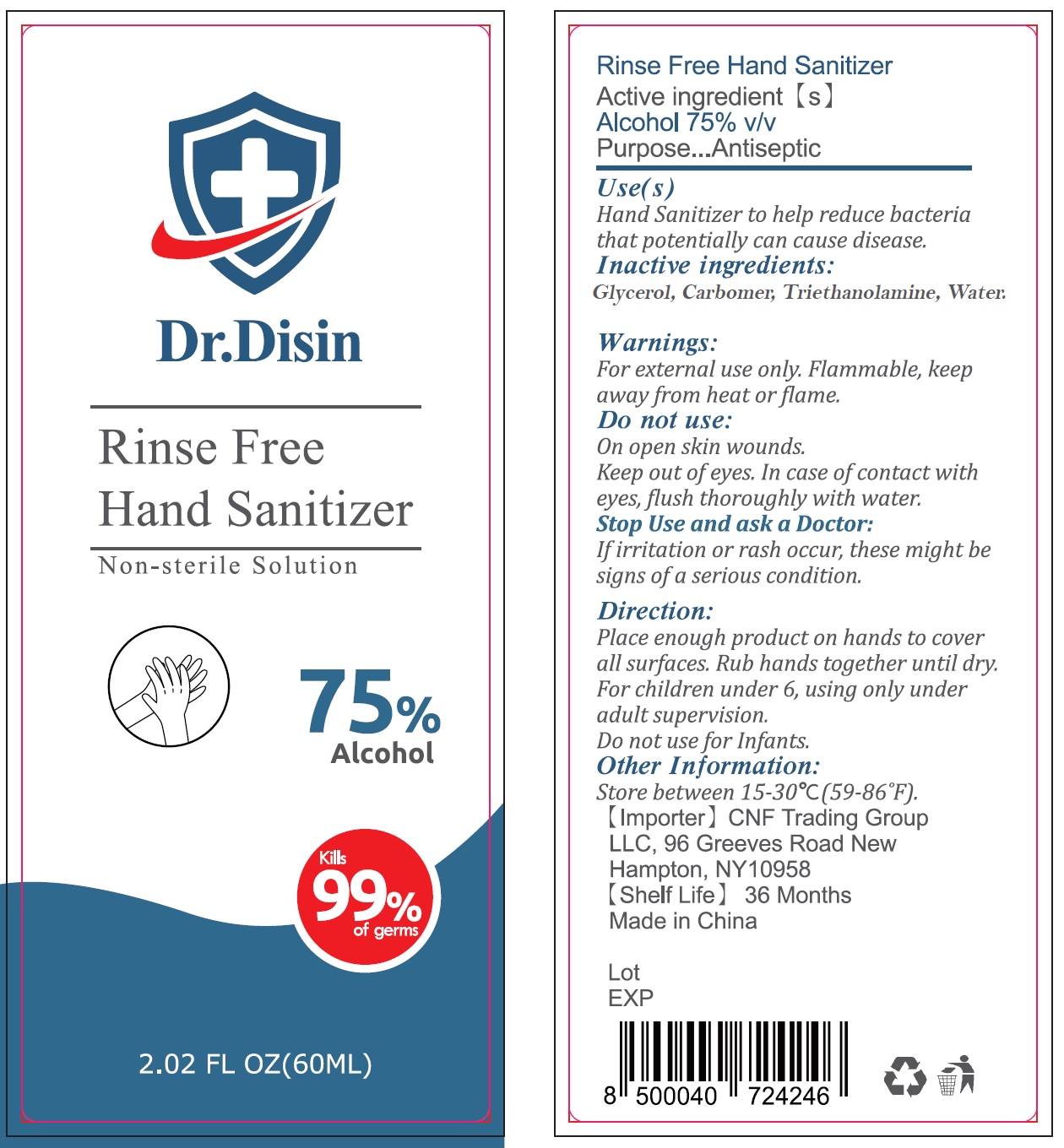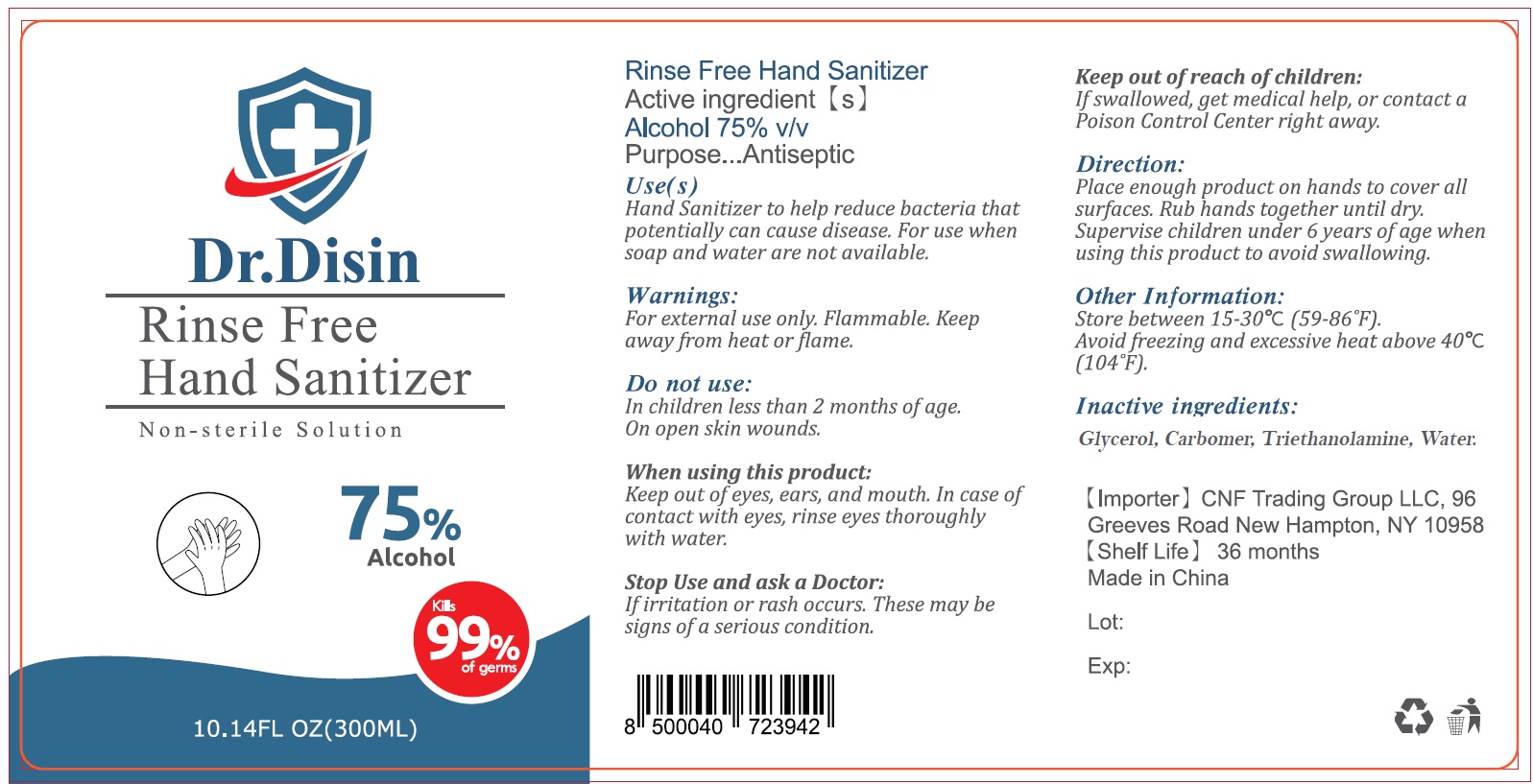 DRUG LABEL: Dr. Disin Hand Sanitizer
NDC: 79205-000 | Form: GEL
Manufacturer: CNF Trading Group
Category: otc | Type: HUMAN OTC DRUG LABEL
Date: 20201020

ACTIVE INGREDIENTS: ALCOHOL 0.75 mL/1 mL
INACTIVE INGREDIENTS: GLYCERIN; CARBOMER HOMOPOLYMER, UNSPECIFIED TYPE; TROLAMINE; WATER

Dr. Disin Hand Sanitizer

Active ingredient [s]

Alcohol 75% v/v

Purpose

Antiseptic

Use(s)

Hand Sanitizer to help reduce bacteria that potentially can cause disease. For use when soap and water are not available.

Warnings:

For external use only. Flammable, keep away from heat or flame.

Do not use:

In children less than 2 months of age. On open skin wounds.

When using this product:

Keep out of eyes, ears, and mouth. In case of contact with eyes, rinse eyes thoroughly with water.

Stop Use and ask a doctor:

If irritation or rash occur, These may be signs of a serious condition.

Keep out of reach of children:

If swallowed, get medical help or contact a Poison Control Center right away.

Directions:

Place enough product on hands to cover all surfaces. Rub hands together until dry. Supervise children under 6 years of age when using this product to avoid swallowing.

Other Information:

Store between 15-30°C (59-86°F).

Avoid freezing and excessive heat above 40°C (104°F).

Inactive ingredients:

Glycerol, Carbomer, Triethanolamine, Water.